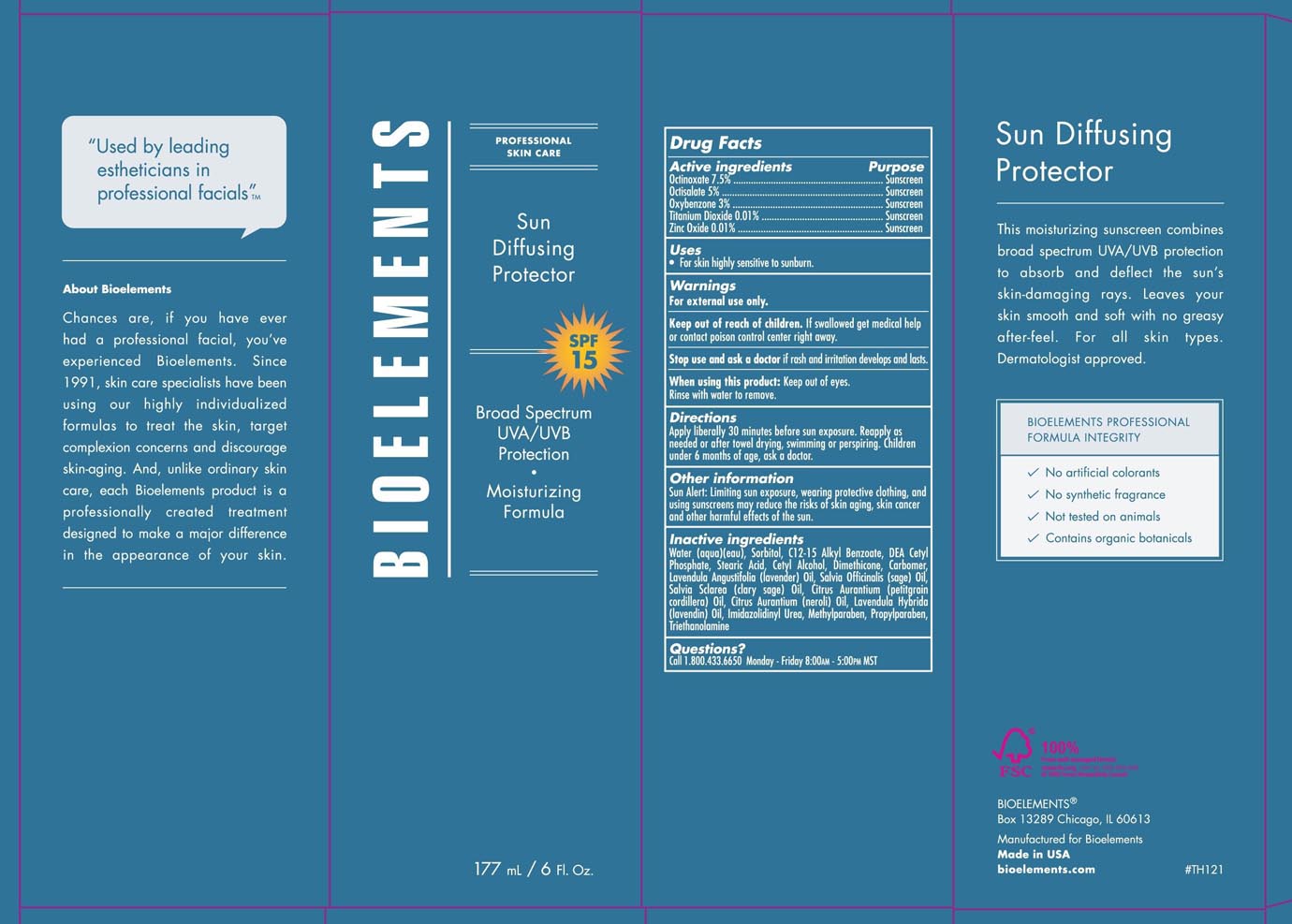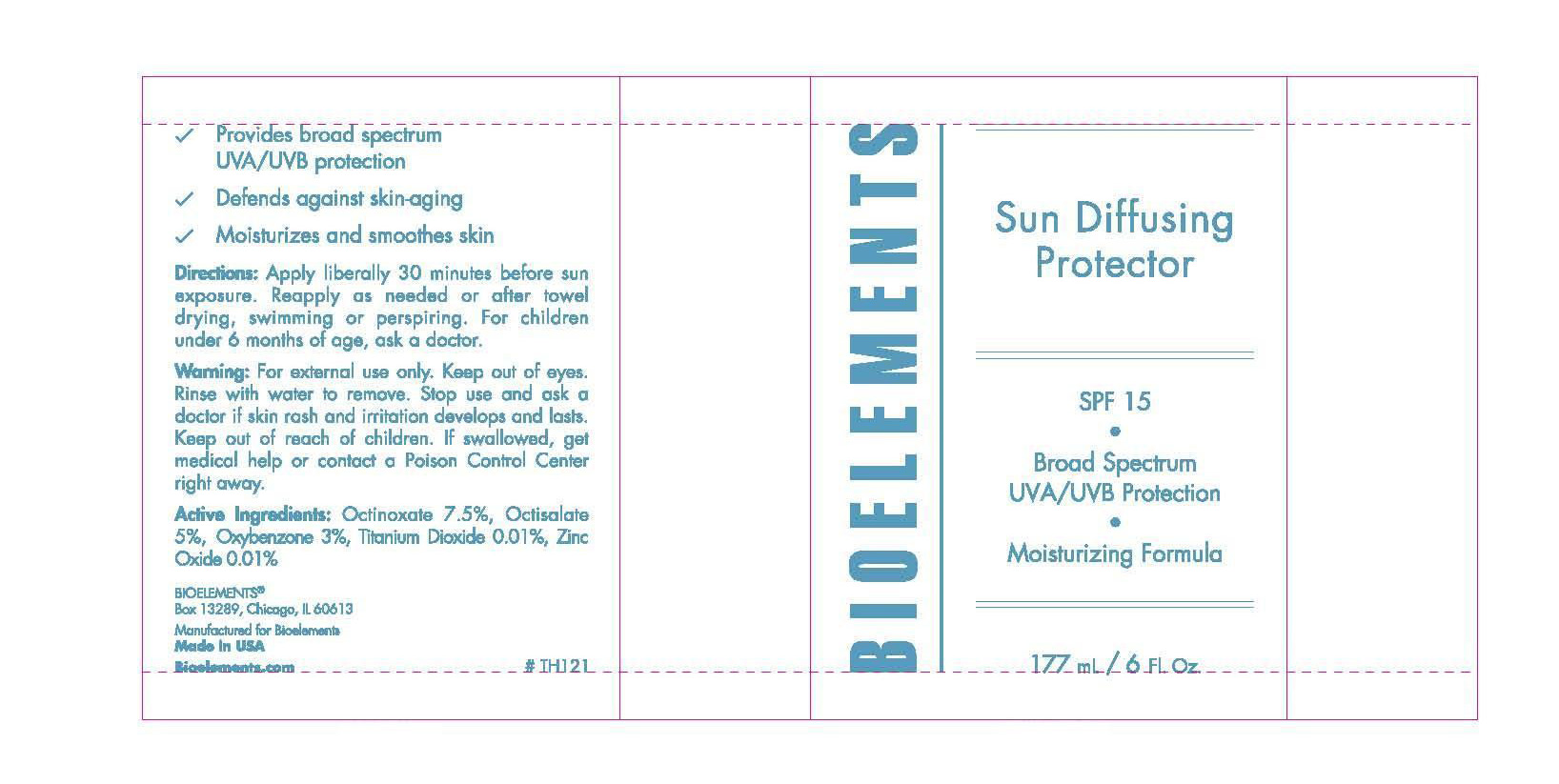 DRUG LABEL: Bioelements
NDC: 49825-114 | Form: CREAM
Manufacturer: Bioelements Inc.
Category: otc | Type: HUMAN OTC DRUG LABEL
Date: 20120112

ACTIVE INGREDIENTS: OCTINOXATE 7.5 mL/100 mL; OCTISALATE 5 mL/100 mL; OXYBENZONE 3 mL/100 mL; TITANIUM DIOXIDE 0.01 mL/100 mL; ZINC OXIDE 0.01 mL/100 mL
INACTIVE INGREDIENTS: SORBITOL; ALKYL (C12-15) BENZOATE; STEARIC ACID; CETYL ALCOHOL; DIMETHICONE; LAVENDER OIL; SAGE OIL; CITRUS AURANTIUM FRUIT OIL; CITRUS AURANTIUM FLOWER OIL; IMIDUREA; METHYLPARABEN; PROPYLPARABEN; TROLAMINE

Sun Diffusing Protector SPF 15

Active Ingredients Purpose

Octinoxate 7.5 % Sunscreen

Octisalate 5% Sunscreen

Oxybenzone 3% Sunscreen

Titanium Dioxide 0.01% Sunscreen

zinc Oxide 0.01% Sunscreen

Uses

For skin highly sensitive to sunburn

Keep out of reach of children. If swallowed get medical help or contact poison control center right away.

Stop use and ask a doctor if rash and irritation develops and lasts

Warnings

For external use only.

When using this product: keep out of eyes. Rinse with water to remove.

Directions

Apply liberally 30 minutes before sun exposure. Reapply as needed or after towel drying, swimming or perspiring. Children under 6 months, ask a doctor.

Inactive Ingredients
Water (aqua) (eau), sorbitol, c12-15 alkyl benzoate, DEA cetyl phosphate, stearic acid, cetyl alcohol, dimethicone, carbomer, Lavendula Augustifolia (Lavender) oil, Salvia Officinalis (sage) Oil, Salvia sclarea (clary sage) oil, Citrus aurantium (petitgrain cordillera) oil, Citrus Aurantium (neroli) oil, Lavendula Hybridia (Lavendin) Oil, Imidazolidinyl Urea, Methylparaben, Propylparaben, Triethanolamine.

PACKAGE LABEL

Sun Diffusing Protector SPF 15

Broad Spectrum UVA/UVB protection

Moisturizing Formula

177 mL / 6 Fl. Oz.